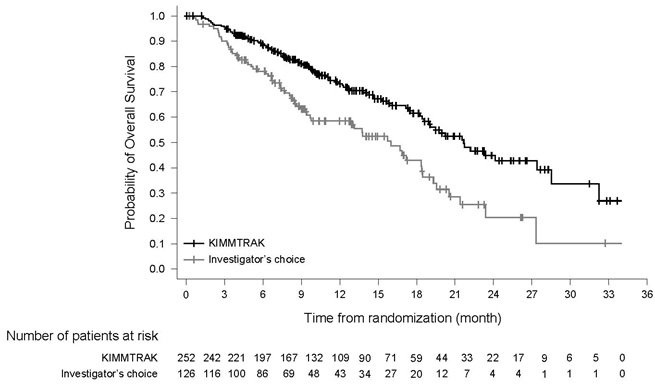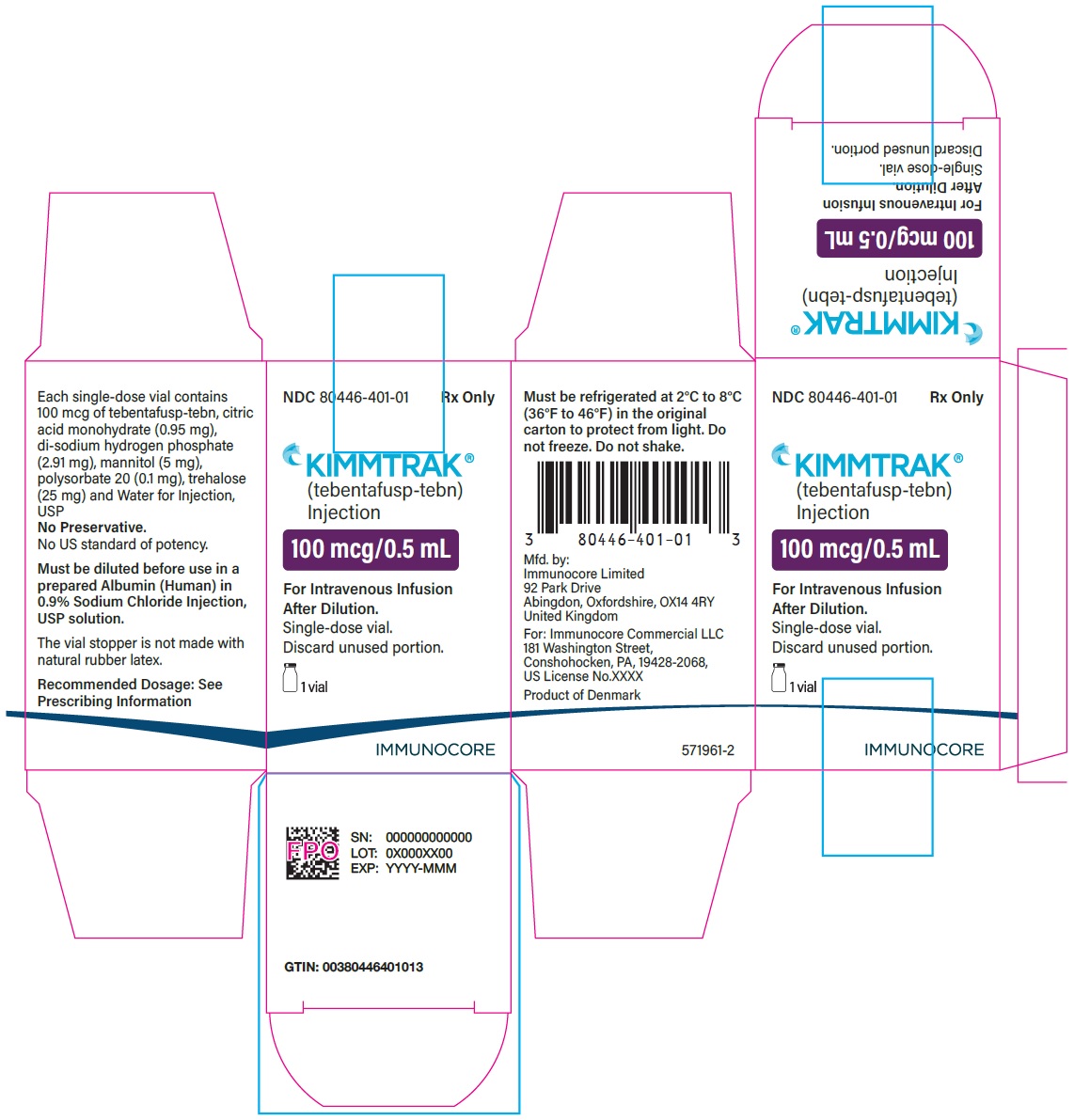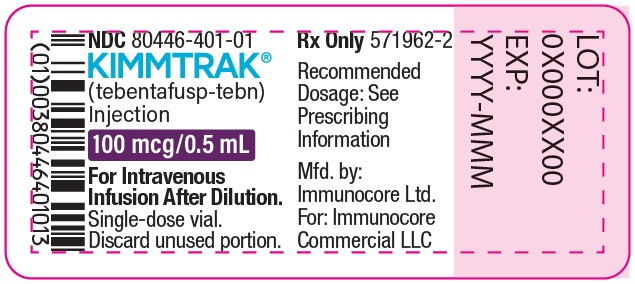 DRUG LABEL: KIMMTRAK
NDC: 80446-401 | Form: INJECTION, SOLUTION, CONCENTRATE
Manufacturer: Immunocore Commercial LLC
Category: prescription | Type: HUMAN PRESCRIPTION DRUG LABEL
Date: 20250506

ACTIVE INGREDIENTS: TEBENTAFUSP 100 ug/0.5 mL

HIGHLIGHTS OF PRESCRIBING INFORMATION

These highlights do not include all the information needed to use KIMMTRAK® safely and effectively. See full prescribing information for KIMMTRAK®.
KIMMTRAK® (tebentafusp-tebn) injection, for intravenous use
Initial U.S. Approval: 2022

WARNING: CYTOKINE RELEASE SYNDROME

Cytokine Release Syndrome (CRS), which may be serious or life-threatening, occurred in patients receiving KIMMTRAK. Monitor for at least 16 hours following first three infusions and then as clinically indicated (2.2, 5.1).

1 INDICATIONS AND USAGE

KIMMTRAK is a bispecific gp100 peptide-HLA-directed CD3 T cell engager indicated for the treatment of HLA-A*02:01-positive adult patients with unresectable or metastatic uveal melanoma (1, 2.1).

2 DOSAGE AND ADMINISTRATION

- Recommended dosage: 20 mcg intravenously on Day 1, 30 mcg intravenously on Day 8, 68 mcg intravenously on Day 15, and 68 mcg intravenously once every week thereafter (2.2).
- Dilute and administer by intravenous infusion over 15-20 minutes (2.2, 2.4).
- See Full Prescribing Information for instructions on preparation and administration of the diluted solution for intravenous infusion (2.2, 2.4).
- Dosage interruption or permanent discontinuation may be required based on individual safety and tolerability (2.3).

3 DOSAGE FORMS AND STRENGTHS

Injection: 100 mcg/0.5 mL solution in a single-dose vial (3).

4 CONTRAINDICATIONS

None (4).

5 WARNINGS AND PRECAUTIONS

- Skin reactions: Rash, pruritus, and cutaneous edema occurred in patients treated with KIMMTRAK. If skin reactions occur, treat based on persistence and severity of symptoms (2.3, 5.2).
- Elevated liver enzymes: Elevations in liver enzymes occurred in patients treated with KIMMTRAK. Monitor ALT, AST, and total bilirubin (2.3, 5.3).
- Embryo-Fetal toxicity: May cause fetal harm. Advise patients of reproductive potential of the potential risk to the fetus and to use effective contraception (5.4, 8.1, 8.3).

6 ADVERSE REACTIONS

The most common adverse reactions (occurring in ≥ 30%) are cytokine release syndrome, rash, pyrexia, pruritus, fatigue, nausea, chills, abdominal pain, edema, hypotension, dry skin, headache and vomiting (6.1). The most common laboratory abnormalities (occurring in ≥50%) are decreased lymphocyte count, increased creatinine, increased glucose, increased aspartate aminotransferase, increased alanine aminotransferase, decreased hemoglobin, and decreased phosphate (6.1).

To report SUSPECTED ADVERSE REACTIONS, contact Immunocore at 1-844-IMMUNO1 (1-844-466-8661) or FDA at 1-800-FDA-1088 or www.fda.gov/medwatch.

FULL PRESCRIBING INFORMATION

WARNING: CYTOKINE RELEASE SYNDROME

Cytokine Release Syndrome (CRS), which may be serious or life-threatening, occurred in patients receiving KIMMTRAK. Monitor for at least 16 hours following first three infusions and then as clinically indicated [(see Dosage and Administration (2.2), see Warnings and Precautions (5.1)].

1 INDICATIONS AND USAGE

KIMMTRAK is indicated for the treatment of HLA-A*02:01-positive adult patients with unresectable or metastatic uveal melanoma.

2 DOSAGE AND ADMINISTRATION

2.1 Patient Selection

Select patients for treatment of unresectable or metastatic uveal melanoma with KIMMTRAK based on a positive HLA-A*02:01 genotyping test of a whole blood sample [see Clinical Studies (14)]. Information on FDA-approved tests is available at http://www.fda.gov/companiondiagnostics.

2.2 Recommended Dosage

The recommended dosage of KIMMTRAK administered intravenously is:

- 20 mcg on Day 1
- 30 mcg on Day 8
- 68 mcg on Day 15
- 68 mcg once every week thereafter

Treat patients until unacceptable toxicity or disease progression occur.

Administer the first three infusions of KIMMTRAK in an appropriate healthcare setting by intravenous infusion over 15-20 minutes. Monitor patients during the infusion and for at least 16 hours after the infusion is complete.

If the patient does not experience Grade 2 or worse hypotension (requiring medical intervention) during or after the third infusion, administer subsequent doses in an appropriate ambulatory care setting, and monitor patients for a minimum of 30 minutes following each of these infusions [see Warnings and Precautions (5.1)].

2.3 Dosage Modifications for Adverse Reactions

No dosage reduction for KIMMTRAK is recommended. Dosage modifications for KIMMTRAK for adverse reactions are summarized in Table 1.

Table 1: Dose Modifications for Adverse Reactions

Adverse Reaction | Severity | KIMMTRAK Dosage Modifications
Cytokine Release Syndrome (CRS) [see Warnings and Precautions (5.1)] | Moderate defined as temperature ≥ 38°C with; - Hypotension that responds to fluids (does not require vasopressors) or - Hypoxia requiring low flow nasal canula (≤ 6 L/min) or blow-by oxygen | - If hypotension and hypoxia do not improve within 3 hours or CRS worsens, escalate care and manage according to next higher level of severity - For moderate CRS that is persistent (lasting 2-3 hours) or recurrent, administer corticosteroid premedication (e.g. dexamethasone 4 mg or equivalent) at least 30 minutes prior to next dose
Cytokine Release Syndrome (CRS) [see Warnings and Precautions (5.1)] | Severe defined as temperature ≥ 38°C with; - Hemodynamic instability requiring a vasopressor (with or without vasopressin) or - Worsening hypoxia or respiratory distress requiring high flow nasal canula (> 6 L/min oxygen) or face mask | - Withhold KIMMTRAK until CRS and sequelae have resolved - Administer intravenous corticosteroid (e.g., 2 mg/kg/day methylprednisolone or equivalent) - Resume KIMMTRAK at same dose level (i.e., do not escalate if severe CRS occurred during initial dose escalation; resume escalation once dosage is tolerated) - For severe CRS, administer corticosteroid premedication (e.g. dexamethasone 4 mg or equivalent) at least 30 minutes prior to next dose
Cytokine Release Syndrome (CRS) [see Warnings and Precautions (5.1)] | Life threatening defined as temperature ≥ 38°C with; - Hemodynamic instability requiring multiple vasopressors (excluding vasopressin) - Worsening hypoxia or respiratory distress despite oxygen administration requiring positive pressure | - Permanently discontinue KIMMTRAK - Administer intravenous corticosteroid (e.g., 2 mg/kg/day methylprednisolone or equivalent)
Skin Reactions [see Warnings and Precautions (5.2)] | Grade 2 or 3a | - Withhold KIMMTRAK until ≤ Grade 1 or baseline - Resume KIMMTRAK at same dose level (i.e., do not escalate if Grade 3 skin reactions occurred during initial dose escalation; resume escalation once dosage is tolerated) - For persistent reactions not responding to oral steroids, consider intravenous corticosteroid (e.g., 2 mg/kg/day methylprednisolone or equivalent)
Skin Reactions [see Warnings and Precautions (5.2)] | Grade 4a | - Permanently discontinue KIMMTRAK - Administer intravenous corticosteroid (e.g., 2 mg/kg/day methylprednisolone or equivalent)
Elevated Liver Enzymes [see Warnings and Precautions (5.3)] | Grade 3 or 4a | - Withhold KIMMTRAK until ≤ Grade 1 or baseline. - Resume KIMMTRAK at same dose level if the elevated liver enzymes occur in the setting of Grade 3 CRS; resume escalation if next administration is tolerated. - If the elevated liver enzymes occur outside the setting of Grade 3 CRS - resume escalation if the current dose is less than 68 mcg, - or resume at same dose level if dose escalation has completed - Administer intravenous corticosteroids if no improvement within 24 hours
Other Adverse Reactions [see Adverse Reactions (6.1)] | Grade 3a | - Withhold KIMMTRAK until ≤ Grade 1 or baseline - Resume KIMMTRAK at same dose level (i.e., do not escalate if other Grade 3 adverse reaction occurred during initial dose escalation; resume escalation once dosage is tolerated)
Other Adverse Reactions [see Adverse Reactions (6.1)] | Grade 4a | - Permanently discontinue KIMMTRAK
a Based on National Cancer Institute Common Terminology Criteria for Adverse Events (CTCAE) version 4.03 (NCI CTCAEv4.03).

2.4 Preparation and Administration

Preparation

- A 2-step dilution process is required for preparation of the final KIMMTRAK dose for infusion.
- Use aseptic technique for dilution and preparation of intravenous infusion solutions.
- Visually inspect parenteral drug products and infusion bags for particulate matter and discoloration prior to administration, whenever solution and container permit.

Step 1: Preparation of the Infusion Bag

To prevent adsorption of tebentafusp-tebn to the infusion bag and other components of the drug delivery system, prepare an Albumin (Human) in 0.9% Sodium Chloride Injection, USP solution as follows:

1. Using a 1 mL syringe with graduations of 2 decimal places and a sterile needle, withdraw the calculated volume of Albumin (Human) into the syringe (see Table 2 below) and add to the 100 mL 0.9% Sodium Chloride Injection, USP bag constructed of polyolefins (PO) [such as polyethylene (PE) and polypropylene (PP)] or polyvinyl chloride (PVC) to make a final Albumin (Human) concentration of 250 mcg/mL.
  Table 2: Examples of Albumin (Human) Concentration and Volumes
  Albumin (Human) concentration* | Albumin (Human) volume for addition to a 100 mL 0.9% Sodium Chloride Injection, USP Infusion Bag to prepare a concentration of 250 mcg/mL Albumin (Human) in 0.9% Sodium Chloride Injection, USP
  5% (50 g/L) | 0.5 mL
  20% (200 g/L) | 0.13 mL
  25% (250 g/L) | 0.1 mL
  *Albumin (Human); use concentration as per local availability. Examples include but are not restricted to the following strengths: 5%, 20%, or 25%.
2. Gently homogenize the prepared solution by completing the following steps:
  1. Invert the infusion bag so that the bag is upside down with the entry port positioned on top. Then tap the side of the port tubing to ensure that any residual solution is released into the bulk solution.
  2. Mix the prepared solution by gently rotating the bag lengthwise 360 degrees from the inverted position at least 5 times. Do not shake the infusion bag.
  3. Repeat (i) and (ii) an additional three times.

Step 2- Preparation of KIMMTRAK Solution for Infusion

1. Do not shake the KIMMTRAK vial.
2. Using a 1 mL syringe with graduations of 2 decimal places and a sterile needle, withdraw the required volume of KIMMTRAK 100 mcg/ 0.5 mL as per the dose required (shown in Table 3 below) and add to the prepared 100 mL infusion bag containing 0.9% Sodium Chloride Injection, USP plus Albumin (Human).
3. Discard the single-dose vial containing the unused portion of KIMMTRAK in accordance with local requirements. Do not prepare more than one dose from the vial.
  Table 3: KIMMTRAK Volumes Required for Addition to the Infusion Bag
  Day of treatment | Dose (mcg) of KIMMTRAK | Volume (mL) of KIMMTRAK
  Day 1 | 20 | 0.1
  Day 8 | 30 | 0.15
  Day 15 and weekly thereafter | 68 | 0.34
4. Mix the infusion bag by following the same procedure outlined in Step 1b.

Administration

- Immediately administer the diluted solution via intravenous infusion over 15-20 minutes through a dedicated intravenous line. A sterile, non-pyrogenic, low protein binding 0.2 micron in-line filter infusion set should be used. Administer the entire contents of the KIMMTRAK infusion bag.
- Administer the prepared infusion bag within 4 hours from the time of preparation including the duration of infusion. During the 4-hour window, the KIMMTRAK infusion bag should remain at room temperature.
- If not used immediately, store the KIMMTRAK infusion bag in a refrigerator at 2°C to 8°C (36°F to 46°F) and infuse within 24 hours from the time of preparation, which includes the storage time in the refrigerator, the time allowed for equilibration of the infusion bag to room temperature, and the duration of the infusion.
- Once removed from the refrigerator, do not refrigerate KIMMTRAK infusion bag again. Do not freeze. Discard unused KIMMTRAK solution beyond the recommended storage time.
- Do not mix KIMMTRAK with other drugs or administer other drugs through the same intravenous line.
- Upon completion of KIMMTRAK infusion, flush the infusion line with adequate volume of sterile 0.9% Sodium Chloride Injection, USP to ensure that the entire contents of the infusion bag are administered.

3 DOSAGE FORMS AND STRENGTHS

Injection: 100 mcg/0.5 mL clear, colorless to slightly yellowish solution in a single-dose vial

4 CONTRAINDICATIONS

None.

5 WARNINGS AND PRECAUTIONS

5.1 Cytokine Release Syndrome

Cytokine release syndrome (CRS), which may be life threatening, occurred in patients receiving KIMMTRAK. Manifestations of CRS may include fever, hypotension, hypoxia, chills, nausea, vomiting, rash, elevated transaminases, fatigue, and headache. CRS (≥ Grade 2) occurred in 77% of patients in Study IMCgp100-202 who received KIMMTRAK [see Adverse Reactions (6.1)]. Among patients who received KIMMTRAK, 23% received systemic corticosteroids for at least 1 infusion, 8% received supplemental oxygen during at least 1 infusion, and 0.8% received a vasopressor for at least 1 infusion. CRS led to permanent discontinuation in 1.2% of patients.

In Study IMCgp100-202, 60% of patients experienced ≥ Grade 2 CRS with more than 1 infusion, with the median number of events being 2 (range 1 - 12). The majority (84%) of episodes of CRS started the day of infusion. Among cases that resolved, the median time to resolution of CRS was 2 days.

Ensure that healthcare providers administering KIMMTRAK have immediate access to medications and resuscitative equipment to manage CRS. Ensure patients are euvolemic prior to initiating the infusions. Closely monitor patients for signs or symptoms of CRS following infusions of KIMMTRAK [see Dosage and Administration (2.2)].

Monitor fluid status, vital signs, and oxygenation level and provide appropriate therapy. Withhold or discontinue KIMMTRAK depending on persistence and severity of CRS [see Dosage and Administration (2.3)].

5.2 Skin Reactions

Skin reactions, including rash, pruritus, and cutaneous edema occurred in patients treated with KIMMTRAK. In study IMCgp100-202, skin reactions occurred in 91% of patients treated with KIMMTRAK, including Grade 2 (44%) and Grade 3 (21%) events. Skin reactions included rash (83%), pruritus (69%), erythema (25%), and cutaneous edema (27%) [see Adverse Reactions (6.1)].

The median time to onset of skin reactions was 1 day (range: 1 – 55 days). The median time to improvement to ≤ Grade 1 was approximately 6 days.

Monitor patients for skin reactions. If skin reactions occur, treat with antihistamine and topical or systemic steroids based on persistence and severity of symptoms. Withhold or permanently discontinue KIMMTRAK depending on the severity of skin reactions [see Dosage and Administration (2.3)].

5.3 Elevated Liver Enzymes

In Study IMCgp100-202, increases in alanine aminotransferase or aspartate aminotransferase were observed in 65% of patients treated with KIMMTRAK.

In patients experiencing ALT/AST elevations, 73% initially occurred within the first 3 infusions with KIMMTRAK. Most patients experiencing Grade 3 or 4 ALT/AST elevations had improvement to ≤ Grade 1 within 7 days. For events that were observed outside the setting of CRS, the median time to onset was 129 days. Grade 3 or greater elevations in liver enzymes outside the setting of CRS occurred in approximately 8% of patients.

Elevations in liver enzymes led to permanent discontinuation in 0.4% of patients receiving KIMMTRAK.

Monitor alanine aminotransferase (ALT), aspartate aminotransferase (AST), and total blood bilirubin prior to the start of and during treatment with KIMMTRAK. Withhold KIMMTRAK according to severity [see Dosage and Administration (2.3)].

5.4 Embryo-Fetal Toxicity

Based on the mechanism of action, KIMMTRAK may cause fetal harm when administered to a pregnant woman. Advise pregnant women of the potential risk to the fetus. Advise females of reproductive potential to use effective contraception during treatment with KIMMTRAK and for 1 week after the last dose [see Use in Specific Populations (8.1, 8.3)].

6 ADVERSE REACTIONS

The following serious adverse reactions are discussed in greater detail in other sections of the label:

- Cytokine Release Syndrome [see Boxed Warning, Warnings and Precautions (5.1)]
- Skin Reactions [see Warnings and Precautions (5.2)]
- Elevated Liver Enzymes [see Warnings and Precautions (5.3)]

6.1 Clinical Trials Experience

Because clinical trials are conducted under widely varying conditions, adverse reaction rates observed in the clinical trials of a drug cannot be directly compared to rates in the clinical trials of another drug and may not reflect the rates observed in practice.

First line metastatic uveal melanoma

The safety of KIMMTRAK was evaluated in study IMCgp100-202, a randomized (2:1), open-label, active-controlled trial in patients who had not received prior systemic therapy for metastatic or advanced uveal melanoma [see Clinical Studies (14)]. Patients received either KIMMTRAK administered at 20 mcg intravenously on Day 1, 30 mcg intravenously on Day 8, 68 mcg intravenously on Day 15, and 68 mcg intravenously once every week thereafter (N=245) or investigator’s choice treatment (N=111). The median duration of exposure was 5.3 months (range: 0.3 to 33 months) in patients treated with KIMMTRAK.

Serious adverse reactions occurred in 28% of patients who received KIMMTRAK. Serious adverse reactions occurring in ≥ 2% of patients were cytokine release syndrome (10%), rashes (4.5%), pyrexia (2.4%), and hypotension (2%). One patient (0.4%) experienced a fatal adverse reaction (pulmonary embolism).

Adverse reactions led to permanent discontinuation in 3.3% of patients who received KIMMTRAK. Adverse reactions that led to permanent discontinuation of KIMMTRAK were anaphylactic reaction, brain edema, cytokine release syndrome, fatigue, hepatotoxicity, hypotension, and nausea (each 0.4%).

Adverse reactions resulting in dosage interruption occurred in 25% of patients who received KIMMTRAK. Adverse reactions which required dosage interruption in ≥ 2% of patients included fatigue (3.7%), lipase increased (2.9%), pyrexia (2.4%), alanine aminotransferase increase (2%), and aspartate aminotransferase increase (2%).

Adverse reactions leading to dose reduction occurred in 5% of patients who received KIMMTRAK. Adverse reactions which required dosage reduction in ≥ 2% of patients were cytokine release syndrome (2.4%), and rashes (2%).

The most common adverse reactions (≥30%) in patients who received KIMMTRAK were cytokine release syndrome, rash, pyrexia, pruritus, fatigue, nausea, chills, abdominal pain, edema, hypotension, dry skin, headache, and vomiting. The most common (≥50%) laboratory abnormalities in patient who received KIMMTRAK were decreased lymphocyte count, increased creatinine, increased glucose, increased AST, increased ALT, decreased hemoglobin, and decreased phosphate.

Table 4 summarizes the adverse reactions observed in study IMCgp100-202.

Table 4: Adverse Reactions (≥20%) in Patients with Metastatic Uveal Melanoma Who Received KIMMTRAK in Study IMCgp100-202

Adverse Reactions | KIMMTRAK (N=245) |  | Investigator’s Choice (pembrolizumab, or ipilimumab, or dacarbazine) (N=111)
 | All Grades (%) | Grade 3 or 4 (%) | All Grades (%) | Grade 3 or 4 (%)
Immune system disorders
Cytokine release syndromea | 89 | 0.8 | 2.7 | 0
Skin and subcutaneous tissue disorders
Rashb | 83 | 18 | 28 | 0
Pruritus | 69 | 4.5 | 23 | 0
Dry skin | 31 | 0 | 3.6 | 0
Skin Hypopigmentationb | 28 | NA | 5 | NA
Erythema | 24 | 0 | 0.9 | 0
Hair color changesb | 20 | NA | 0 | NA
General disorders and administration site conditions
Pyrexia | 76 | 3.7 | 7 | 0.9
Fatigueb | 64 | 6 | 42 | 0.9
Chills | 48 | 0.4 | 3.6 | 0
Edemab | 45 | 0 | 10 | 0
Gastrointestinal disorders
Nausea | 49 | 2 | 26 | 0.9
Abdominal painb | 45 | 2.9 | 33 | 3.6
Vomiting | 30 | 1.2 | 9 | 0
Diarrhea | 25 | 1.2 | 20 | 2.7
Vascular disorders
Hypotension | 39 | 3.3 | 2.7 | 0
Nervous system disorders
Headache | 31 | 0.4 | 10 | 0.9
Musculoskeletal and connective tissue disorders
Arthralgia | 22 | 0.8 | 16 | 0
a Represents algorithmic identification of CRS cases based on ASTCT grading criteria (Lee et al. 2019).
b Represents a composite of multiple related terms.

Clinically relevant adverse reactions occurring in < 20% of patients who received KIMMTRAK included back pain, decreased appetite, constipation, hypertension, tachycardia or sinus tachycardia, dyspnea, paresthesia, dizziness, flushing, muscle spasms, myalgia, pain in extremity, alopecia, skin hyperpigmentation, influenza-like illness, oropharyngeal pain and night sweats.

Table 5 summarizes the selected laboratory abnormalities observed in study IMCgp100-202.

Table 5: Selected Laboratory Abnormalities (≥ 10%) worsening from baseline in patients who received KIMMTRAK versus Investigator’s Choice
 | KIMMTRAKa (N=245) |  | Investigator’s Choicea (pembrolizumab, or ipilimumab, or dacarbazine) (N=111)
 | Grades 1-4 (%) | Grades 3-4 (%) | Grades 1-4 (%) | Grades 3-4 (%)
HEMATOLOGY
Lymphocyte count decreased | 91 | 56 | 26 | 1.8
Hemoglobin decreased | 51 | 0.8 | 20 | 0.9
Platelet count decreased | 16 | 0 | 15 | 0.9
Neutrophil count decreased | 14 | 2 | 8 | 1.8
CHEMISTRY
Creatinine increased | 87 | 0.4 | 73 | 0
Glucose increased | 66 | 3.3 | 39 | 4.6
AST increased | 55 | 13 | 39 | 1.9
ALT increased | 52 | 9 | 29 | 1.8
Phosphate decreased | 51 | 11 | 20 | 2
Albumin decreased | 47 | 2.1 | 14 | 0.9
Calcium decreased | 45 | 1.6 | 15 | 1.9
Lipase increased | 37 | 15 | 28 | 6
Magnesium decreased | 34 | 0 | 8 | 0
Alk phos increased | 34 | 2.9 | 36 | 1.8
Sodium decreased | 30 | 2.9 | 15 | 0.9
Potassium increased | 29 | 1.6 | 15 | 0.9
Bilirubin increased | 27 | 4.1 | 14 | 7
Amylase increased | 23 | 4.1 | 18 | 1
Glucose decreased | 18 | 0.4 | 4.6 | 0
Potassium decreased | 17 | 0.8 | 8 | 0.9
Calcium increased | 13 | 0 | 3.7 | 0
Alk Phos = Alkaline Phosphatase; AST=aspartate aminotransferase; ALT=alanine aminotransferase
a The denominator used to calculate the rate varied from 242 to 245 for KIMMTRAK and 105 to 109 for IC based on the number of patients with a baseline value and at least one post-treatment value for the laboratory assessment.

8 USE IN SPECIFIC POPULATIONS

8.1 Pregnancy

Risk Summary

Based on the mechanism of action, KIMMTRAK may cause fetal harm when administered to a pregnant woman [see Clinical Pharmacology (12.1)]. There are no available data with KIMMTRAK in pregnant woman. No animal reproductive and developmental toxicity studies have been conducted with KIMMTRAK. Molecules of similar molecular weight can cross the placenta resulting in fetal exposure. Advise women of the potential risk to the fetus.

In the U.S. general population, the estimated background risk of major birth defects and miscarriage in clinically recognized pregnancies is 2%-4% and 15%-20%, respectively.

8.2 Lactation

Risk Summary

There are no data on the presence of tebentafusp-tebn in human milk, the effect on the breastfed child, or the effects on milk production. Because tebentafusp-tebn may be excreted in human milk and because of the potential for serious adverse reactions in a breastfed child, advise patients not to breastfeed during treatment with KIMMTRAK and for at least 1 week after the last dose.

8.3 Females and Males of Reproductive Potential

KIMMTRAK may cause fetal harm when administered to a pregnant woman [see Use in Specific Populations (8.1)].

Pregnancy Testing

Verify pregnancy status in females of reproductive potential prior to initiating KIMMTRAK treatment.

Contraception

Females

Advise female of reproductive potential to use effective contraception during treatment and for 1 week following the last dose of KIMMTRAK [see Use in Specific Populations (8.1)].

8.4 Pediatric Use

Safety and efficacy of KIMMTRAK have not been established in pediatric patients.

8.5 Geriatric Use

Of the 245 patients with metastatic uveal melanoma treated with KIMMTRAK on IMCgp100-202, 47% were 65 years of age and older and 9% were 75 years of age and older. No overall differences in safety or efficacy were observed between patients ≥ 65 years of age compared to younger adult patients.

11 DESCRIPTION

Tebentafusp-tebn is a bispecific gp100 peptide-HLA-directed T cell receptor CD3 T cell engager. Tebentafusp-tebn has an approximate molecular weight of 77 kDa. Tebentafusp-tebn is produced by recombinant DNA technology in Escherichia coli cells.

KIMMTRAK (tebentafusp-tebn) injection is supplied in a single-dose vial as a sterile, preservative-free, clear, colorless or slightly yellowish solution for intravenous administration by infusion.

Each single-dose vial contains tebentafusp-tebn (100 mcg), citric acid monohydrate (0.95 mg), di-sodium hydrogen phosphate (2.91 mg), mannitol (5 mg), polysorbate 20 (0.1 mg) trehalose (25 mg), and water for injection, with a pH of 6.5.

12 CLINICAL PHARMACOLOGY

12.1 Mechanism of Action

Tebentafusp-tebn is a bispecific gp100 peptide-HLA-A*02:01 directed T cell receptor CD3 T cell engager. The TCR arm binds to a gp100 peptide presented by human leukocyte antigen-A*02:01 (HLA-A*02:01) on the cell surface of uveal melanoma tumor cells.

In vitro, tebentafusp-tebn bound to HLA-A*02:01-positive uveal melanoma cells and activated polyclonal T cells to release inflammatory cytokines and cytolytic proteins, which results in direct lysis of uveal melanoma tumor cells.

12.2 Pharmacodynamics

Lymphocyte counts declined the day after the first 3 doses and returned to baseline prior to subsequent doses.

Serum levels of cytokines (IFN-γ, TNFα, IL-2, IL-6, IL-10 and IL-1RA) and chemokines (CXCL9, CXCL10, CXCL11, hepatocyte growth factor, and monocyte chemoattractant protein-1) were increased during the first three doses of KIMMTRAK with peak levels between 8 to 24 hours after treatment with KIMMTRAK and levels returned to baseline prior to subsequent doses. In subsequent treatment cycles, cytokine elevation occurred in fewer patients with lesser intensity compared to the first 3 doses.

The exposure-response relationship and time course of pharmacodynamic response for the safety and effectiveness of KIMMTRAK have not been fully characterized.

12.3 Pharmacokinetics

After a single dose administration, tebentafusp-tebn Cmax and AUC0-7d increased in an approximately dose proportional manner from 20 to 68 mcg (0.3 to 1 times the approved recommended dose). Following administration of the approved recommended dosage in patients with metastatic uveal melanoma, the steady-state geometric mean (% CV) Cmax of tebentafusp-tebn is 13 ng/mL (34.6%) and AUC0-7d is 4.6 ng.day/mL (23%) with no accumulation.

Distribution

Tebentafusp-tebn geometric mean (% CV) steady-state volume of distribution is 7.56 L (24%).

Elimination

The geometric mean clearance of tebentafusp-tebn is 16.4 L/d (CV: 24.5%) and median terminal half-life is 7.5 hours (range: 6.8-7.5 hours).

Metabolism

Tebentafusp-tebn is expected to be catabolized into small peptides and amino acids.

Specific Populations

No clinically significant difference in the pharmacokinetics of tebentafusp-tebn were identified based on weight (43 to 163 kg), sex (48% female), age (23 to 91 years), or mild to moderate renal impairment based on creatinine clearance (CLcr) estimated by C-G formula (CLcr 30 to 89 mL/min) or mild hepatic impairment as measured by total bilirubin (TB) and aspartate aminotransferase (AST) (TB ≤ upper limit of normal (ULN) and AST > ULN or TB > 1 to 1.5x ULN and any AST).

Tebentafusp-tebn has not been studied in patients with severe (CLcr < 30 mL/min) renal impairment or in patients with moderate (TB >1.5 to 3x ULN, any AST) to severe (TB > 3 to 10x ULN, any AST) hepatic impairment.

Drug Interaction

Elevation of certain proinflammatory cytokines may suppress CYP450 enzyme activities.

12.6 Immunogenicity

The observed incidence of anti-drug antibodies is highly dependent on the sensitivity and specificity of the assay. Differences in assay methods preclude meaningful comparisons of the incidence of anti-drug antibodies in the studies described below with the incidence of anti-drug antibodies in other products or studies, including those of KIMMTRAK.

In studies IMCgp100-102 and IMCgp100-202, 36% (47/131) and 28% (67/240) of patients who were treated with tebentafusp-tebn at the recommended dosing regimen for up to 29 cycles and 45 cycles, respectively, developed anti-tebentafusp-tebn antibodies (ADA). Among the patients who developed ADAs, neutralizing antibodies (NAb) against tebentafusp-tebn were detected in 57% (27/47) and 63% (42/67), respectively, in studies IMCgp100-102 and IMCgp100-202. The median onset time to ADA formation was 8 and 12 weeks and 15 and 16 weeks for NAb formation after tebentafusp-tebn treatment in studies IMCgp100-102 and IMCgp100-202, respectively.

Tebentafusp-tebn exposure was lower in the presence of ADAs and NAbs. In Studies IMCgp100-102 and IMCgp100-202, tebentafusp-tebn treated patients who developed ADAs had tebentafusp-tebn concentrations (Cmax) that were 50% to 99% lower compared to patients who did not develop ADAs. Tebentafusp-tebn clearance was higher in patients with high titer ADAs (titers > 8192), resulting in a lower exposure (AUC0-7 days) by 97% compared to patients who did not develop ADA, and terminal half-life decreased to 10-14 minutes. Development of high titer Nabs (titers >100 in Study IMCgp100-102 or >640 in Study IMCgp100-202) resulted in lower Cmax of tebentafusp-tebn by 85% to 99% compared to patients who did not develop NAbs, and the tebentafusp-tebn concentrations (Cmax) became undetectable in 43.5% (30/69) of patients who developed NAbs in both studies.

The effect of ADA and NAb on pharmacodynamics, safety, or effectiveness of tebentafusp-tebn has not been fully characterized.

13 NONCLINICAL TOXICOLOGY

13.1 Carcinogenesis, Mutagenesis, Impairment of Fertility

No carcinogenicity or genotoxicity studies have been conducted with tebentafusp-tebn.

No studies have been conducted to evaluate the effects of tebentafusp-tebn on fertility.

14 CLINICAL STUDIES

Study IMCgp100-202: First line metastatic uveal melanoma

KIMMTRAK was evaluated in IMCgp100-202, a randomized, open-label, multicenter trial (NCT03070392) that enrolled patients with metastatic uveal melanoma (N=378). Patients were required to be HLA-A*02:01 genotype positive identified by a central assay. Patients were excluded if they received prior systemic therapy for metastatic or advanced uveal melanoma or localized liver-directed therapy. Prior surgical resection of oligometastatic disease was permitted. Patients with clinically significant cardiac disease or the presence of symptomatic or untreated brain metastasis were excluded.

Patients were randomized (2:1) to receive KIMMTRAK weekly by intravenous infusion administered at 20 mcg intravenously on Day 1, 30 mcg intravenously on Day 8, 68 mcg intravenously on Day 15, and 68 mcg intravenously once every week thereafter (N=252) or Investigator’s choice (N=126) of pembrolizumab, ipilimumab, or dacarbazine. Randomization was stratified by lactate dehydrogenase (LDH) level at study entry. Across both arms, patients stopped treatment for disease progression, unless the patient was otherwise deriving benefit, or for unacceptable toxicity.

The major efficacy outcome was overall survival (OS). Additional efficacy outcomes were investigator-assessed progression free survival (PFS) and objective response rate (ORR) per RECIST 1.1.

The median age was 64 years (range 23 to 92 years); 50% were female; 87% were White, and 12% were unreported or unknown race. The reported ethnicity was Hispanic or Latino in 2.4% of patients. Baseline ECOG performance status was 0 (73%), 1 (21%), or 2 (0.3%); 36% had elevated LDH level; and 94% had liver metastasis.

The efficacy results are summarized in Table 6 and Figure 1.

Table 6: Efficacy Results in Study IMCgp100-202

 | KIMMTRAK (N=252) | Investigator’s Choice (pembrolizumab, or ipilimumab, or dacarbazine) (N=126)
Overall Survival (OS)^1
Number of deaths | 87 (34.5%) | 63 (50%)
Median in months (95% CI) | 21.7 (18.6, 28.6) | 16 (9.7, 18.4)
HR (95% CI)^2 | 0.51 (0.37, 0.71)
p-value^(3, 4) | <0.0001
Progression-free Survival^5
Number (%) of patients with event | 198 (78.6%) | 97 (77%)
Median in months (95% CI) | 3.3 (3, 5) | 2.9 (2.8, 3)
HR (95% CI)^2 | 0.73 (0.58, 0.94)
p-value^(3, 6) | 0.0139
Objective Response Rate (95% CI)^7 | 9.1% (5.9, 13.4) | 4.8% (1.8, 10.1)
Complete Response | 1 (0.4%) | 0
Partial Response | 22 (8.7%) | 6 (4.8%)
CI= Confidence Interval, HR= Hazard Ratio
^1 Based on prespecified interim analysis
^2 Hazard ratio is from a cox proportional hazards model stratified by LDH status
^3 Two-sided p-value based on log rank test stratified by LDH
^4 Compared to the interim efficacy boundary of 0.006
^5 Final PFS analysis
^6 Compared to the efficacy boundary of 0.05.
^7 Not formally tested

Figure 1: Kaplan-Meier Curves of Overall Survival in Study IMCgp100-202

16 HOW SUPPLIED/STORAGE AND HANDLING

How Supplied

Each KIMMTRAK (tebentafusp-tebn) injection carton (NDC 80446-401-01) contains:

- One single-dose vial containing 100 mcg of tebentafusp-tebn in 0.5 mL of sterile, preservative-free, clear, colorless or slightly yellowish solution.

The vial stopper is not made with natural rubber latex.

Storage and Handling

- Store KIMMTRAK vials in the original carton refrigerated at 2°C to 8°C (36°F to 46°F) and protect from light until time of use. Do not freeze. Do not shake.

17 PATIENT COUNSELING INFORMATION

Advise the patient to read the FDA-approved patient labeling (Patient Information).

Cytokine Release Syndrome (CRS)

Inform patients of the risk of CRS, and to immediately contact their healthcare provider for signs and symptoms associated with CRS (e.g., pyrexia, hypotension, hypoxia, chills, nausea, vomiting, fatigue, or headache) [see Warnings and Precautions (5.1)].

Skin Reactions

Inform patients that rashes and skin reactions have occurred in patients who have received KIMMTRAK. Advise patients to contact their healthcare provider for signs and symptoms of progressive or intolerable skin reactions [see Warnings and Precautions (5.2)].

Elevated Liver Enzymes

Inform patients that elevations in liver enzymes have occurred in patients who have received KIMMTRAK. Advise patients to contact their healthcare provider for signs and symptoms of liver toxicity (e.g., right sided abdominal pain, jaundice, scleral icterus) [see Warnings and Precautions (5.3)].

Embryo-Fetal Toxicity

- Advise females to inform their healthcare provider if they are pregnant or become pregnant. Inform females of the risk to a fetus [see Warnings and Precautions (5.4) and Use in Specific Populations (8.1)].
- Advise females of reproductive potential to use effective contraception while on KIMMTRAK and for 1 week after the last dose [see Use in Specific Populations (8.1) and (8.3)].

Lactation

- Advise patients not to breastfeed during treatment with KIMMTRAK and for 1 week after the last dose [see Use in Specific Populations (8.2)].

Manufactured by:
Immunocore Limited
92 Park Drive, Milton Park
Abingdon, Oxfordshire
United Kingdom, OX144RY
License no: 2239

At:
Baxter Oncology GmbH
Kantstraβe 2
33790 Halle/Westfalen
Germany

For:
Immunocore Commercial LLC
181 Washington Street,
Conshohocken, PA, US

PATIENT INFORMATION

KIMMTRAK®(KIM-track)
(tebentafusp-tebn)
Injection

What is the most important information I should know about KIMMTRAK?

KIMMTRAK can cause serious side effects that can be severe or, life threatening, and usually happens within the first three infusions. These side effects include:

- Cytokine Release Syndrome (CRS). Tell your healthcare provider right away if you get any of the following symptoms:
  - fever
  - tiredness or weakness
  - vomiting
  - chills
  - nausea
  - low blood pressure
  - dizziness and light headedness
  - headache
  - wheezing and trouble breathing
  - rash

Your healthcare provider will check for these problems during treatment with KIMMTRAK. Your healthcare provider may temporarily stop or completely stop your treatment with KIMMTRAK, if you have severe side effects.

See “What are the possible side effects of KIMMTRAK?” for more information about side effects.

What is KIMMTRAK?

KIMMTRAK is a prescription medicine used to treat HLA-A*02:01-positive adults with uveal melanoma that cannot be removed by surgery or has spread.

Your healthcare provider will test you for a presence of HLA-A*02:01 gene to make sure KIMMTRAK is right for you. It is not known if KIMMTRAK is safe and effective in children.

Before you receive KIMMTRAK, tell your healthcare provider about all of your medical conditions, including if you:

- are pregnant or plan to become pregnant. KIMMTRAK may harm your unborn baby. Tell your healthcare provider if you become pregnant during treatment with KIMMTRAK.

For females who are able to become pregnant:

- Your healthcare provider should do a pregnancy test before you start treatment with KIMMTRAK.
- Use an effective form of birth control during treatment with KIMMTRAK and for at least 1 week after the last dose of KIMMTRAK.
- are breastfeeding or plan to breastfeed. It is not known if KIMMTRAK passes into your breast milk. Do not breastfeed during the treatment with KIMMTRAK and for at least 1 week after the last dose of KIMMTRAK.

Tell your healthcare provider about all medicines you take, including prescription and over-the-counter medicines, vitamins, and herbal supplements.

How will I receive KIMMTRAK?

- KIMMTRAK will be given to you by intravenous (IV) infusion into your vein for 15 to 20 minutes.
- KIMMTRAK is usually given every week.
- Your healthcare provider will decide how many treatments you need.
- Your healthcare provider will keep you under observation for at least 16 hours following the first three KIMMTRAK treatments and for at least 30 minutes after future treatments.
- Your healthcare provider may delay your treatment of KIMMTRAK if you have certain side effects.
- Your healthcare provider may do blood tests regularly during treatment with KIMMTRAK.

What are the possible side effects of KIMMTRAK?

KIMMTRAK can cause serious side effects, including:

- See "What is the most important information I should know about KIMMTRAK?”.
- Skin reactions. KIMMTRAK may cause skin reactions that require treatment. Tell your healthcare provider if you get symptoms of skin reactions, such as rash, itching, or skin swelling, that are severe and do not go away.
- Abnormal liver blood tests. Your healthcare provider will do blood tests to check your liver before you start KIMMTRAK and during treatment with KIMMTRAK. Tell your healthcare provider if you get symptoms of liver problems such as right-sided abdominal pain or yellowing of the skin or eyes.

The most common side effects of KIMMTRAK include:

- cytokine release syndrome (CRS)
- rash
- fever
- itching
- tiredness
- nausea
- chills
- stomach pain
- swelling
- low blood pressure (symptoms may include dizziness or light headedness)
- dry skin
- headache
- vomiting
- abnormal liver blood tests

These are not all the possible side effects of KIMMTRAK.

Call your healthcare provider for medical advice about side effects. You may report side effects to FDA at 1-800-FDA-1088.

General information about safe and effective use of KIMMTRAK.

Medicines are sometimes prescribed for purposes other than those listed in a Patient Information Leaflet. If you would like more information about KIMMTRAK, talk with your healthcare provider. You can ask your healthcare provider for more information about KIMMTRAK that is written for healthcare professionals.

What are the ingredients in KIMMTRAK?

Active ingredient: tebentafusp

Inactive ingredients: citric acid monohydrate, di-sodium hydrogen phosphate, mannitol, polysorbate 20, trehalose, and Water for injection.

Manufactured by:
Immunocore Limited
92 Park Drive, Milton Park
Abingdon, Oxfordshire
United Kingdom, OX144RY
License no: 2239

at: Baxter Oncology GmbH, Kantstraβe 2, 33790 Halle/Westfalen Germany.

For: Immunocore Commercial LLC 181 Washington Street Conshohocken, PA, US

KIMMTRAK is a trademark of the Immunocore Limited

For more information, go to www.KIMMTRAK.com or call 1-844-IMMUNO1 (1-844-466-8661).

This Patient Information has been approved by the U.S. Food and Drug Administration Issued: January 2022